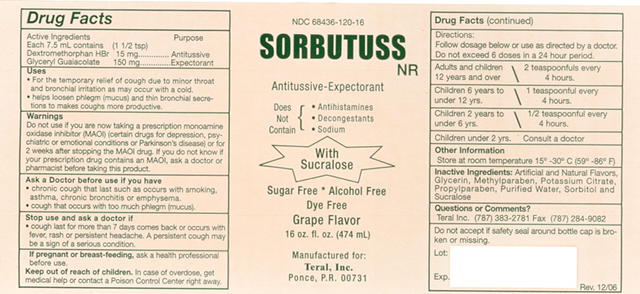 DRUG LABEL: Sorbutuss
NDC: 68436-120 | Form: LIQUID
Manufacturer: Dextrum Laboratories Inc.
Category: otc | Type: HUMAN OTC DRUG LABEL
Date: 20251226

ACTIVE INGREDIENTS: DEXTROMETHORPHAN HYDROBROMIDE 10 mg/5 mL; GUAIFENESIN 100 mg/5 mL
INACTIVE INGREDIENTS: POTASSIUM CITRATE

HIGHLIGHTS OF PRESCRIBING INFORMATION

These highlights do not include all the information needed to use Sorbutuss. See full prescribing information for Initial U.S. Approval
OTC Monograph

These highlights do not include all the information needed to use Sorbutuss. See full prescribing information for Initial U.S. Approval

- For the temporary relief of cough due to minor throat and bronchial irritation as may occur with a cold.
- Helps loosen phlegm (mucus) and thin bronchial secretions to makes cough more productive.

These highlights do not include all the information needed to use

Follow dosage below or use as directed by a doctor. Do not exceed 6 doses in a 24 hours period.

Adults and children 12 years and older 2 teaspoonfuls every 4 hours

Children 6 years to under 6 years 1 teaspoonful every 4 hours

Children 2 years to 6 years 1/2 teaspoonful every 4 hours

Children under 2 years Consult a doctor

FULL PRESCRIBING INFORMATION

Active Ingredients

Each 7.5 mL. Contains (1 1/2 tsp)

Dextromethorphan HBr 15 mg......Antitussive

Glyceryl Guaiacolate 150 mg....Expectorant

Purpose Section

Antitusive

Expectorant

These highlights do not include all the information needed to use Sorbutuss. See full prescribing information for Initial U.S. Approval

- For the temporary relief of cough due to minor throat and bronchial irritation as may occur with a cold.
- Helps loosen phlegm (mucus) and thin bronchial secretions to makes cough more productive.

Warnings

Do not use if you are now taking a prescription monoamine oxidase inhibitor (MAOI) (certain drugs for depression, psychiatric or emotional conditions or Parkinson's disease) or for 2 weeks after stopping the MAOI drug. If you do not know if your prescription drug contains an MAOI, ask a doctor or pharmacist before taking this product.

Ask A Doctor Before use if you have

- Chronic cough that last such as occurs with smoking, asthma, chronic bronchitis or emphysema.
- Cough that occurs with too much phlegm (mucus).

Stop use and ask a doctor if

- Cough last for more than 7 days comes back or occurs with fever, rash or persistent headache. A persistent cough may be a sign of a serious condition.

Pregnancy or breast feeding section

If pregnant or breast-feeding, ask a health professional before use

Keep out of reach of children

In a case of overdose, get medical help or contact a Poison Control Center right away.

These highlights do not include all the information needed to use

Follow dosage below or use as directed by a doctor. Do not exceed 6 doses in a 24 hours period.

Adults and children 12 years and older 2 teaspoonfuls every 4 hours

Children 6 years to under 6 years 1 teaspoonful every 4 hours

Children 2 years to 6 years 1/2 teaspoonful every 4 hours

Children under 2 years Consult a doctor

Other information

Store at room temperature 15º-30º C (59º - 86º F)

Inactive Ingredients

Artificial and Natural Flavors, Glycerin, Methylparaben, Potassium Citrate, Propylparaben, Purified Water, Sorbitol and Sucralose

Questions or Comments?

Teral, Inc. (787) 383-2781 Fax (787) 284-9082

Safety Information

Do not accept if safety seal around bottle cap is broken or missing

Expiration Date information

Lot:

Exp:

Rev:12/06

Principal Panel

NDC 68436-120-16

Sorbutuss NR

Antitussive-Expectorant

Does Not Containt

Antihistamines

Decongestants

Sodium

With

Sucralose

Sugar Free Alcohol Free

Dye Free

Grape Flavor

16 oz. fl. oz. (474 mL)

Manufacture for

Teral, Inc.

Ponce, P.R. 00731